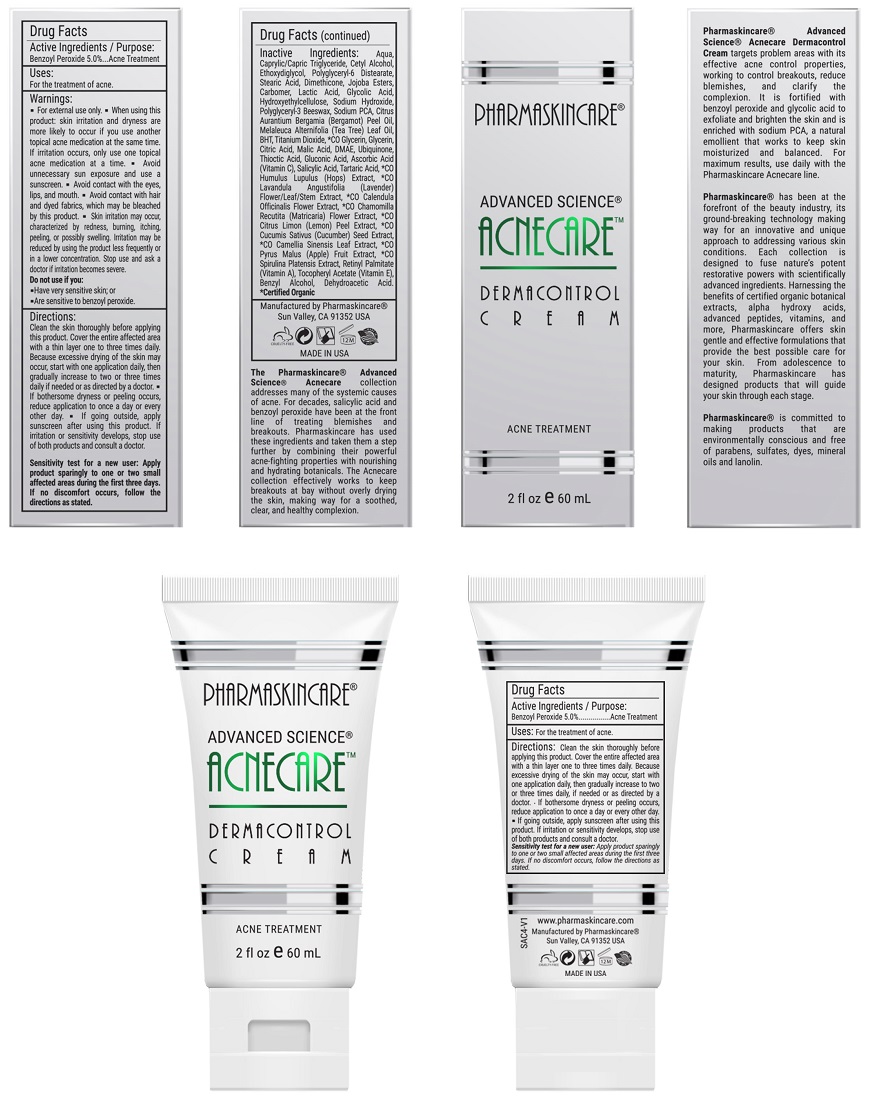 DRUG LABEL: Pharmaskincare Acnecare Dermacontrol Cream
NDC: 68062-9109 | Form: LOTION
Manufacturer: Spa de Soleil
Category: otc | Type: HUMAN OTC DRUG LABEL
Date: 20171011

ACTIVE INGREDIENTS: BENZOYL PEROXIDE 0.063 mg/2.5 mL
INACTIVE INGREDIENTS: CETYL ALCOHOL; WATER; GLYCERIN; MEDIUM-CHAIN TRIGLYCERIDES

Pharmaskincare Acnecare Dermacontrol Cream

Active Ingredient

Benzoyl Peroxide 5.0%

Purpose

Acne Treatment

Warnings

- For external use only.
- When using this product : skin irritation and dryness is more likely to occur if you use another topical acne medication at the same time. If irritation occurs, only use one topical acne medication at a time.
- avoid unnecessary sun exposure and use a sunscreen
- avoid contact with the eyes, lips, and mouth
- avoid contact with hair and dyed fabrics, which may be bleached by this product
- skin irritation may occur, characterized by redness, burning, itching, peeling, or possibly swelling. Irritation may be reduced by using the product less frequently or in a lower concentration. Stop use and ask a doctor if irritation becomes severe

Do not use if you:

● have very sensitive skin

● are sensitive to benzoyl peroxide

Directions

Clean the skin thoroughly before applying this product. Cover the entire affected area with a thin layer and rinse thoroughly one to three times daily. Because excessive drying of the skin may occur, start with one application daily, then gradually increase to two or three times daily if needed or as directed by a doctor.

● If bothersome dryness or peeling occurs, reduce application to once a day or every other day.

● If going outside, apply sunscreen after using this product. If irritation or sensitivity develops, stop use of both products and ask a doctor.

Sensitivity Test for a New User. Apply product sparingly to one or two small affected areas during the first 3 days. If no discomfort occurs, follow the directions stated

Uses:

For the treatment of acne.

Inactive Ingredients:

Water, Stearic Acid, Cetyl Alcohol, Ethoxydiglycol, Caprylic/Capric Triglyceride, Carbomer, Dimethicone, Jojoba Esters, Polyglyceryl-3 Beeswax, Polyglyceryl-6 Distearate, Lactic Acid, Glycolic Acid, Hydroxyethylcellulose, Sodium Hydroxide, Sodium PCA, Citrus Aurantium Bergamia (Bergamot) Peel Oil, Melaleuca Alternifolia (Tea Tree) Leaf Oil, BHT, Titanium Dioxide, *CO Glycerin, Glycerin, Citric Acid, Malic Acid, DMAE, Ubiquinone, Thioctic Acid, Gluconic Acid, Ascorbic Acid (Vitamin C), Malus Domestica Fruit Cell Culture Extract, Salicylic Acid, Tartaric Acid, *CO Humulus Lupulus (Hops) Extract, *CO Lavandula Angustifolia (Lavender) Flower/Leaf/Stem Extract, *CO Calendula Officinalis Flower Extract, *CO Chamomilla Recutita (Matricaria) Flower Extract, *CO Citrus Limon (Lemon) Peel Extract, *CO Cucumis Sativus (Cucumber) Seed Extract, *CO Camellia Sinensis Leaf Extract, *CO Pyrus Malus (Apple) Fruit Extract, *CO Spirulina Platensis Extract, Xanthan Gum, Lecithin, Retinyl Palmitate (Vitamin A), Tocopheryl Acetate (Vitamin E), Benzyl Alcohol, Dehydroacetic Acid

Warning

Keep out of reach of children.

Do not use if you:

● have very sensitive skin

● are sensitive to benzoyl peroxide

PACKAGE LABEL

Pharmaskincare AcnecareDermacontrol.jpg